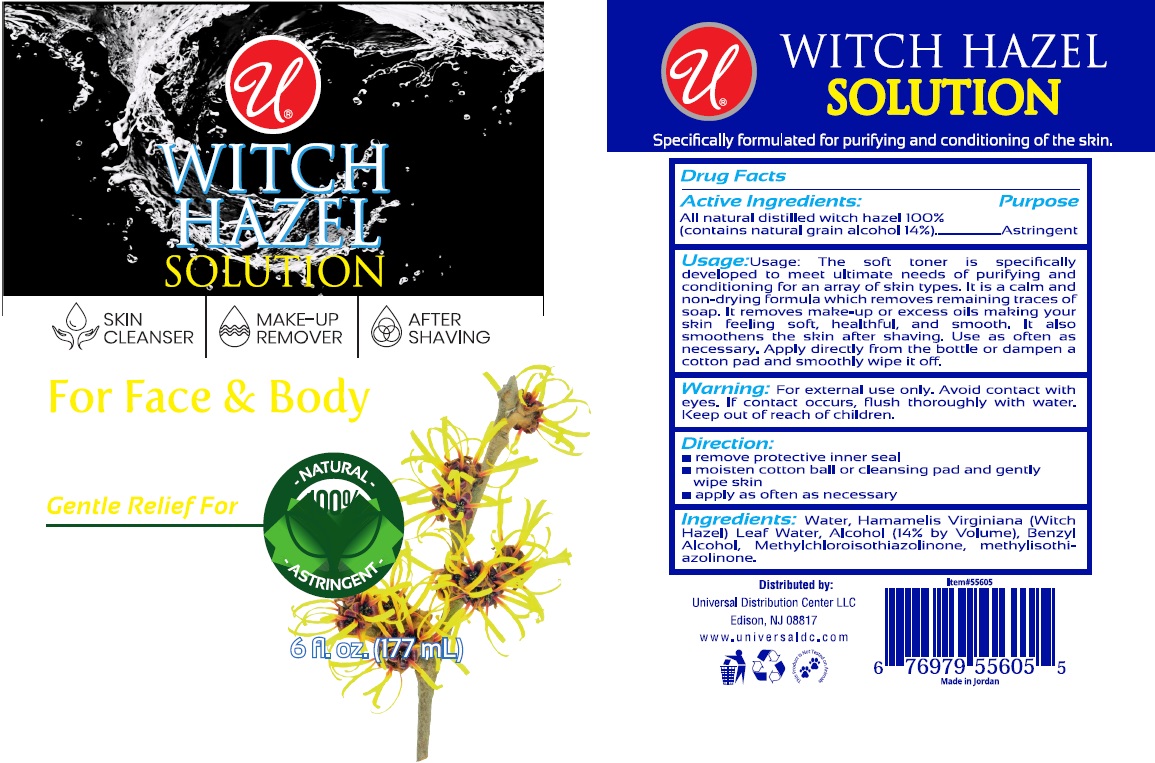 DRUG LABEL: Universal WITCH HAZEL
NDC: 52000-414 | Form: SOLUTION
Manufacturer: Universal Distribution Center LLC
Category: otc | Type: HUMAN OTC DRUG LABEL
Date: 20241212

ACTIVE INGREDIENTS: WITCH HAZEL 3 g/100 mL
INACTIVE INGREDIENTS: WATER; HAMAMELIS VIRGINIANA LEAF WATER; ALCOHOL; BENZYL ALCOHOL; METHYLCHLOROISOTHIAZOLINONE; METHYLISOTHIAZOLINONE

WITCH HAZEL SOLUTION

Active Ingredients:

All natural distilled witch hazel 100%
(contains natural grain alcohol 14%)

Purpose

Astringent

Usage:

The soft toner is specifically developed to meet ultimate needs of purifying and conditioning for an array of skin types. It is a calm and non-drying formula which removes remaining traces of soap. It removes make-up or excess oils making your skin feeling soft, healthful, and smooth. It also smoothens the skin after shaving. Use as often as necessary. Apply directly from the bottle or dampen a cotton pad and smoothly wipe it off.

Warning:

For external use only. Avoid contact with eyes. If contact occurs, flush thoroughly with water.

Keep out of reach of children.

Direction:

• remove protective inner seal
• moisten cotton ball or cleansing pad and gently wipe skin
• apply as often as necessary

Ingredients:

Water, Hamamelis Virginiana (Witch Hazel) Leaf Water, Alcohol (14% by Volume), Benzyl Alcohol, Methylchloroisothiazolinone, methylisothiazolinone.

SKIN CLEANSER

MAKE-UP REMOVER

AFTER SHAVING

For Face & Body

Gentle Relief For

100% NATURAL ASTRINGENT

Specifically formulated for purifying and conditioning of the skin.

Distributed by:
Universal Distribution Center LLC
Edison, NJ 08817
www.universaldc.com

This Product is Not Tested on Animals

Made in Jordan